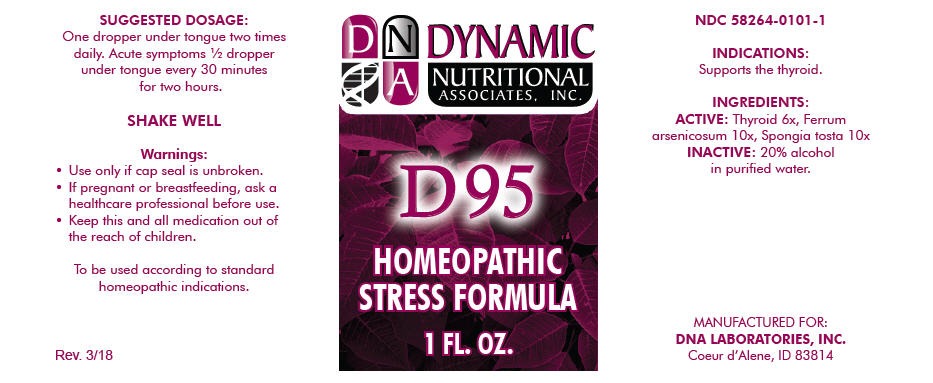 DRUG LABEL: D-95
NDC: 58264-0101 | Form: SOLUTION
Manufacturer: DNA Labs, Inc.
Category: homeopathic | Type: HUMAN OTC DRUG LABEL
Date: 20250113

ACTIVE INGREDIENTS: THYROID, UNSPECIFIED 6 [hp_X]/1 mL; FERROUS ARSENATE 10 [hp_X]/1 mL; SPONGIA OFFICINALIS SKELETON, ROASTED 10 [hp_X]/1 mL
INACTIVE INGREDIENTS: ALCOHOL; WATER

D-95

NDC 58264-0101-1

INDICATIONS

PURPOSE

Supports the thyroid.

INGREDIENTS

ACTIVE

Thyroid 6x, Ferrum arsenicosum 10x, Spongia tosta 10x

INACTIVE

20% alcohol in purified water.

SUGGESTED DOSAGE

One dropper under tongue two times daily. Acute symptoms ½ dropper under tongue every 30 minutes for two hours.

STORAGE AND HANDLING

SHAKE WELL

Warnings

- Use only if cap seal is unbroken.

PREGNANCY OR BREAST FEEDING

- If pregnant or breastfeeding, ask a healthcare professional before use.

KEEP OUT OF REACH OF CHILDREN

- Keep this and all medication out of the reach of children.

To be used according to standard homeopathic indications.

PRINCIPAL DISPLAY PANEL - 1 FL. OZ. Bottle Label

DYNAMIC
NUTRITIONAL
ASSOCIATES, INC.

D 95

HOMEOPATHIC
STRESS FORMULA

1 FL. OZ.